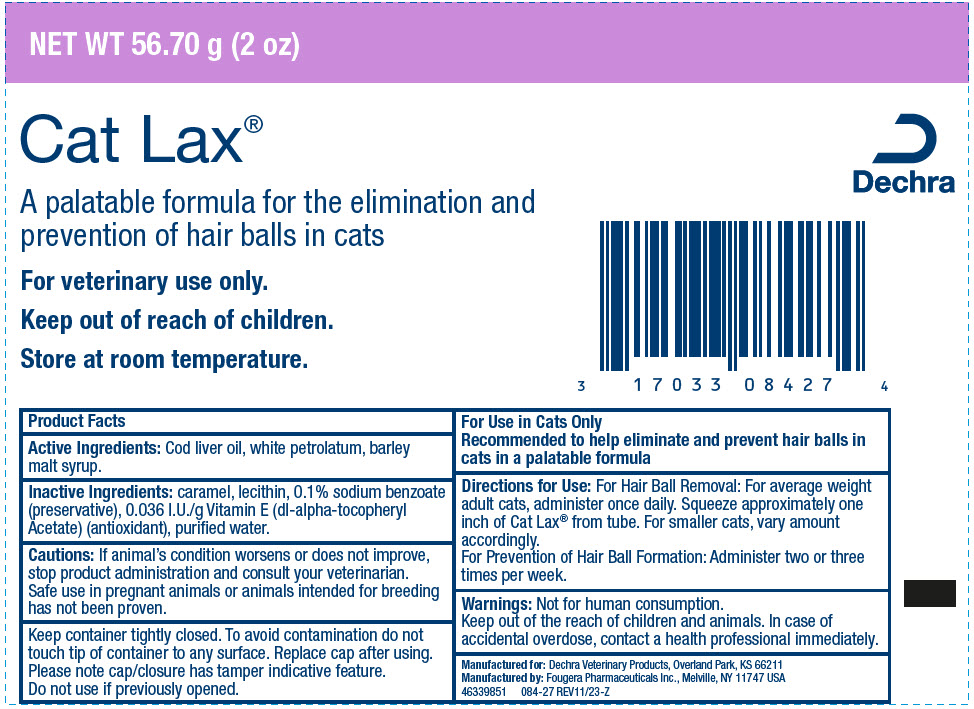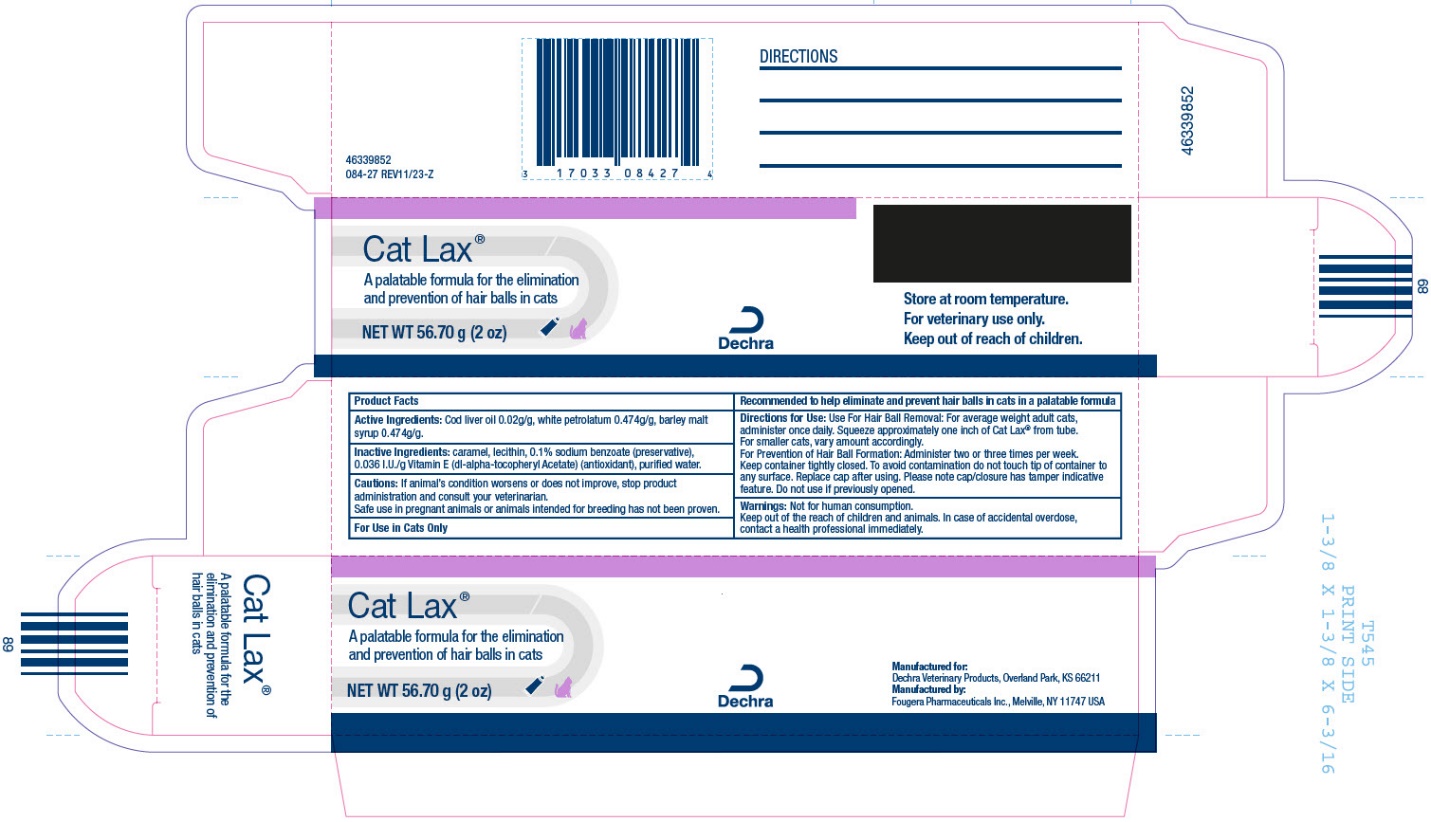 DRUG LABEL: Cat Lax
NDC: 17033-084 | Form: PASTE
Manufacturer: Dechra Veterinary Products
Category: animal | Type: OTC ANIMAL DRUG LABEL
Date: 20220815

ACTIVE INGREDIENTS: PETROLATUM 0.474 g/1 g; BARLEY MALT SYRUP 0.474 g/1 g; COD LIVER OIL 0.02 g/1 g
INACTIVE INGREDIENTS: SODIUM BENZOATE; .ALPHA.-TOCOPHEROL ACETATE; WATER; CARAMEL; LECITHIN, SOYBEAN

Cat Lax®

PURPOSE

A palatable formula for the elimination and prevention of hair balls in cats

For veterinary use only.

Indications and Usage

For Use in Cats Only

Recommended to help eliminate and prevent hair balls in cats in a palatable formula

Active Ingredient

Cod liver oil 0.02g/g, white petrolatum 0.474g/g, barley malt syrup 0.474g/g.

Inactive Ingredients

caramel, lecithin, 0.1% sodium, benzoate, (preservative), 0.036 I.U./g Vitamin E (dl-alpha-tocopheryl Acetate) (antioxidant), purified water.

Cautions

If animal’s condition worsens or does not improve, stop product administration and consult your veterinarian.

Safe use in pregnant animals or animals intended for breeding has not been proven.

Directions for Use

Use For Hair Ball Removal: For average weight adult cats, administer once daily. Squeeze approximately one inch of Cat Lax® from tube.

For smaller cats, vary amount accordingly.

For Prevention of Hair Ball Formation: Administer two or three times per week.

Warnings

Not for human consumption.

Keep out of the reach of children and animals. In case of accidental overdose, contact a health professional immediately.

Storage and Handling

Store at room temperature.

Keep container tightly closed. To avoid contamination do not touch tip of container to any surface. Replace cap after using. Please note cap/closure has tamper indicative feature.

Do not use if previously opened.

Manufacturer

Manufactured for:

Dechra Veterinary Products, Overland Park, KS 66211

Manufactured by:

Fougera Pharmaceuticals Inc., Melville, NY 11747 USA

PRINCIPAL DISPLAY PANEL - 2 oz Tube

NET WT 56.70 g (2 oz)

Cat Lax®

PRINCIPAL DISPLAY PANEL - 2 oz Carton

Cat Lax®

NET WT 56.70 g (2 oz)